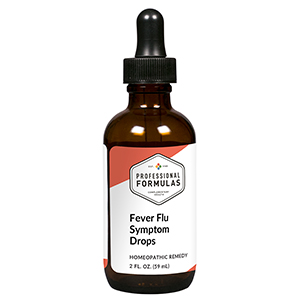 DRUG LABEL: Fever Flu Symptom Drops
NDC: 63083-2087 | Form: LIQUID
Manufacturer: Professional Complementary Health Formulas
Category: homeopathic | Type: HUMAN OTC DRUG LABEL
Date: 20190815

ACTIVE INGREDIENTS: EUPHRASIA STRICTA 2 [hp_X]/59 mL; ULMUS RUBRA BARK 2 [hp_X]/59 mL; SOLANUM DULCAMARA WHOLE 3 [hp_X]/59 mL; FERROSOFERRIC PHOSPHATE 4 [hp_X]/59 mL; RUTA GRAVEOLENS FLOWERING TOP 4 [hp_X]/59 mL; PULSATILLA MONTANA WHOLE 4 [hp_X]/59 mL; EPINEPHRINE 6 [hp_X]/59 mL; BRYONIA ALBA ROOT 6 [hp_X]/59 mL; EUPATORIUM PERFOLIATUM FLOWERING TOP 6 [hp_X]/59 mL; HYSSOPUS OFFICINALIS WHOLE 6 [hp_X]/59 mL; THUJA OCCIDENTALIS LEAF 6 [hp_X]/59 mL; ACONITUM NAPELLUS WHOLE 6 [hp_X]/59 mL; AMARYLLIS BELLADONNA WHOLE 8 [hp_X]/59 mL; CAMPHOR (NATURAL) 12 [hp_X]/59 mL; HAEMOPHILUS INFLUENZAE 12 [hp_X]/59 mL; TOXICODENDRON PUBESCENS LEAF 12 [hp_X]/59 mL
INACTIVE INGREDIENTS: ALCOHOL; WATER

C87

ACTIVE INGREDIENTS

Euphrasia officinalis 2X
Ulmus fulva 2X
Dulcamara 3X
Ferrum phosphoricum 4X
Ruta graveolens 4X
Pulsatilla 4X, 6X, 12X
Adrenalinum 6X
Bryonia 6X
Eupatorium perfoliatum 6X
Hyssopus officinalis 6X
Thuja occidentalis 6X
Aconitum napellus 6X, 8X, 12X
Belladonna 8X
Camphora 12X
Influenzinum 12X
Rhus toxicodendron 12X

QUESTIONS

Professional Formulas

PO Box 2034 Lake Oswego, OR 97035

INDICATIONS

For the temporary relief of flu-like symptoms such as low-grade fever, chills, nasal or chest congestion, occasional headache, or fatigue.*

PURPOSE

*Claims based on traditional homeopathic practice, not accepted medical evidence. Not FDA evaluated.

WARNINGS

Persistent symptoms may be a sign of a serious condition. If symptoms persist or are accompanied by a fever, rash, or persistent headache, consult a doctor. Keep out of the reach of children. In case of overdose, get medical help or contact a poison control center right away. If pregnant or breastfeeding, ask a healthcare professional before use.

Keep out of the reach of children.

PREGNANCY OR BREAST FEEDING

If pregnant or breastfeeding, ask a healthcare professional before use.

DIRECTIONS

Place drops under tongue 30 minutes before/after meals. Adults and children 12 years and over: Take 10 drops up to 3 times per day for up to 6 weeks. For immediate onset of symptoms, take 10 to 15 drops every 15 minutes up to 3 hours. For less severe symptoms, take 10-15 drops hourly up to 8 hours. Consult a physician for use in children under 12 years of age.

OTHER INFORMATION

Tamper resistant. If seal is broken, do not use. After opening, close container tightly and store at room temperature away from heat.

INACTIVE INGREDIENTS

20% ethanol, purified water.

LABEL

Est 1985

Professional Formulas

Complementary Health

Fever Flu Symptom Drops

Homeopathic Remedy

2 FL. OZ. (59 mL)